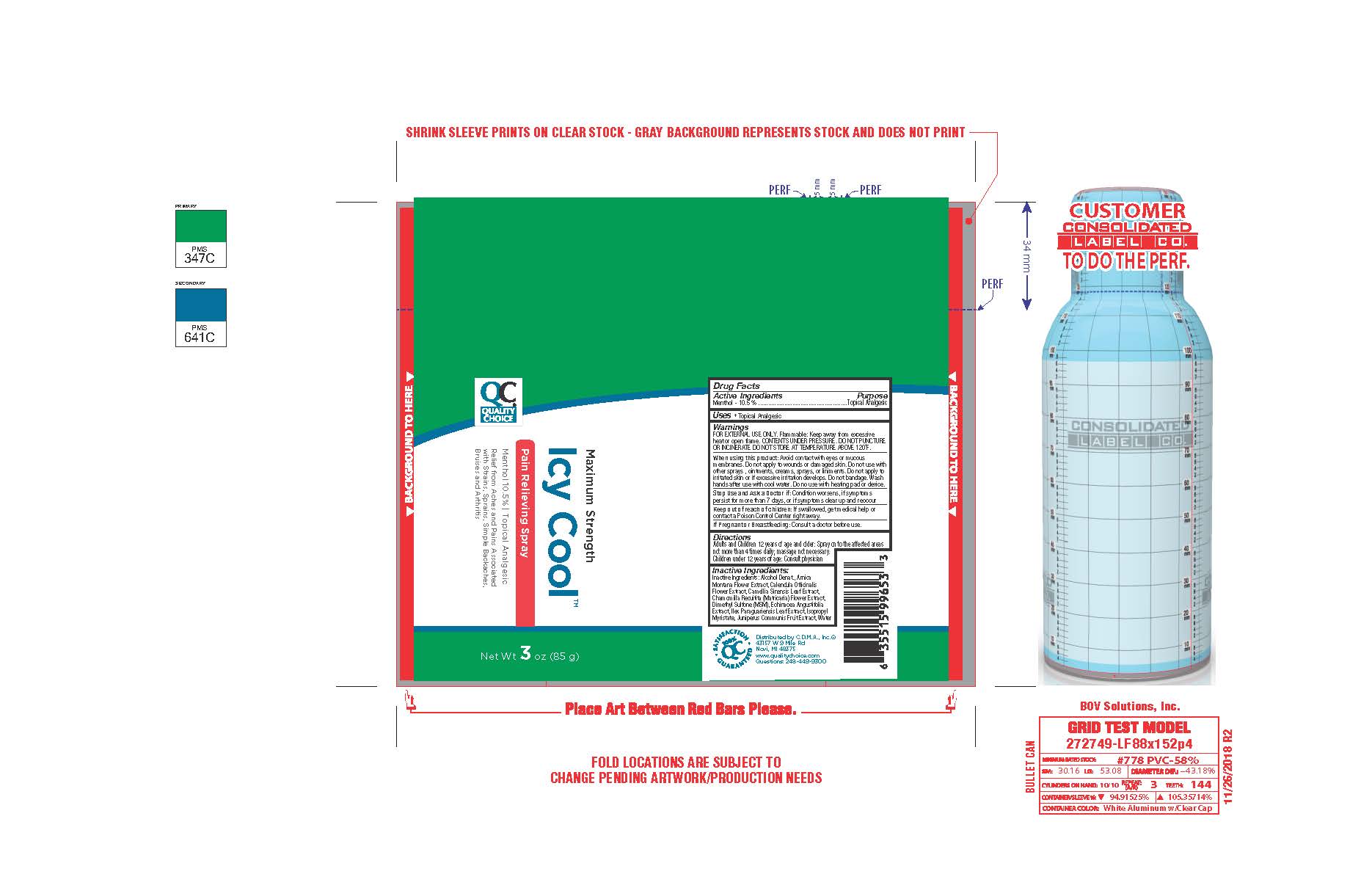 DRUG LABEL: C.D.M.A Icy Cool
NDC: 52313-1131 | Form: SPRAY
Manufacturer: Sklar BOV Solutions Inc
Category: otc | Type: HUMAN OTC DRUG LABEL
Date: 20220131

ACTIVE INGREDIENTS: MENTHOL, UNSPECIFIED FORM 105 mg/1 g
INACTIVE INGREDIENTS: ARNICA MONTANA; CAMELLIA SINENSIS WHOLE; JUNIPERUS COMMUNIS WHOLE; CHAMOMILE; ALCOHOL; DIMETHYL SULFONE; ECHINACEA, UNSPECIFIED; WATER; CALENDULA OFFICINALIS FLOWER; ISOPROPYL MYRISTATE; ILEX PARAGUARIENSIS LEAF

C.D.M.A. Icy Cool

Active Ingredient Purpos

Menthol 10.5% Topical Analgesic

PURPOSE

Uses - Topical Analgesic

INDICATIONS AND USAGE

Temporary relief form minor aches and pains of sore muscles and joints associated with arthritis backache, strains and sprains

Warning

FOR EXTERNAL USE ONLY. Flammaable. Keep away form excessive heat of open flame. CONTENTS UNDER

PRESSURE. DO NOT PUNCTURE OR INCINERATE. DO NOT STORE AT TEMPERATURE ABOVE 120°F.

When using this product; Avoid contact with eyes or mucous membranes. Do not apply to wounds or damages skin.

Do not use with others sprays, ointments, creams, sprays of liniments. Do not apply to irritated skin or if excessive

irritation develops. Do not bandage. Wash hands after use with cold water. Do not use with heating pad or device.

Stop Use and Ask a Doctor if: Condition worsens. If symptoms persist for more than 7 days, of if symptons clean up and

reoccur.

Keep out of reach of Children. If swallowed, het medical help or contact a Poison Control Center right away.

PREGNANCY OR BREAST FEEDING

If Pregnant of Breastfeeding; Consult a doctor before use.

Directions

Adults and Children 12 years of age and older. Spray on the affected areas not more than 4 times daily, massage not

necceeary. Children under 12 years of age, Consult Physicial

Inactive Ingredients:

Inactive Ingredients: Alcohol Denat., Arnica Montana Flower Extract. Calendula Officinalis Flower Extract, Camellia

Sinensis Leaf Extract, Chamomilla Recultita (Matricana) Flower Extract, Dimethyl Sulfone (MSM), Echinacea Augustifola

Extract, Ilex Paraguariensis Leaf Extract, Isopropyl Myristate, Juniperus Communis Fruit Extract, Water

QUESTIONS

Distributed by C.D.M.A. Inc.©

43157 W 9 Mile Rd

Novi, NI 48375

www.qualitychoice.com

Questions: 248-449-9300

PACKAGE LABEL

85 grams NDC52313-1131-1

Maximum Strength

Icy Cool™

Pain Relieving Spray

Menthol 10.5 % | Topical Analgesic

Relief from Aches and Pains Associated with Strains, Sprains, Simple Bachaches, Bruses and Arthritus

Quatity Choice®